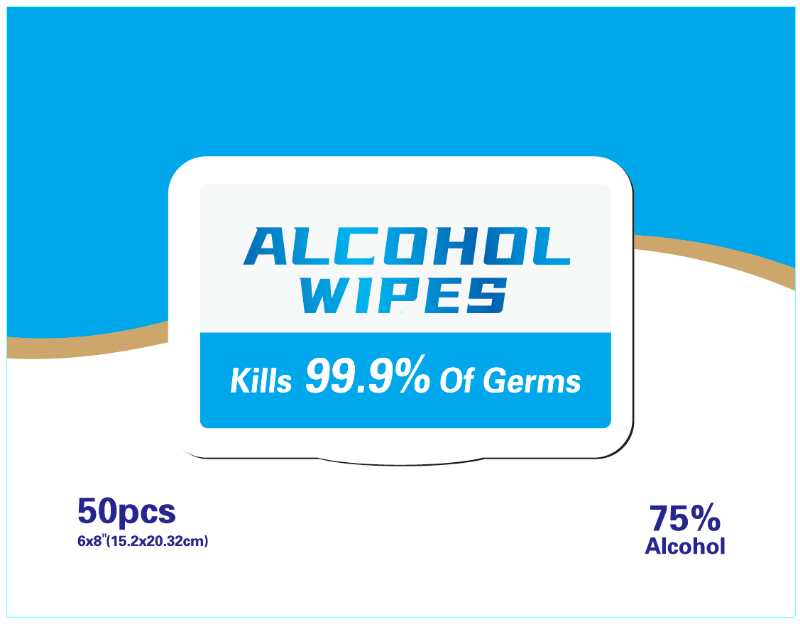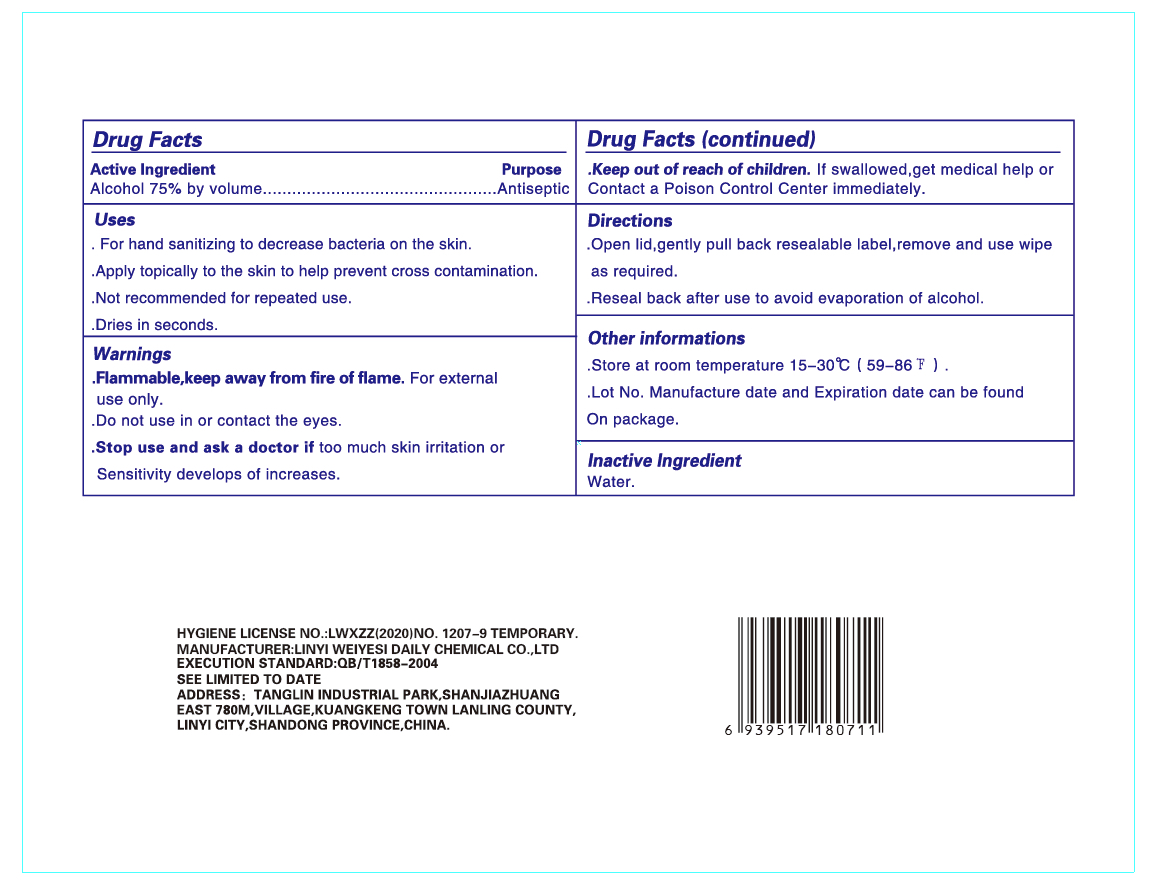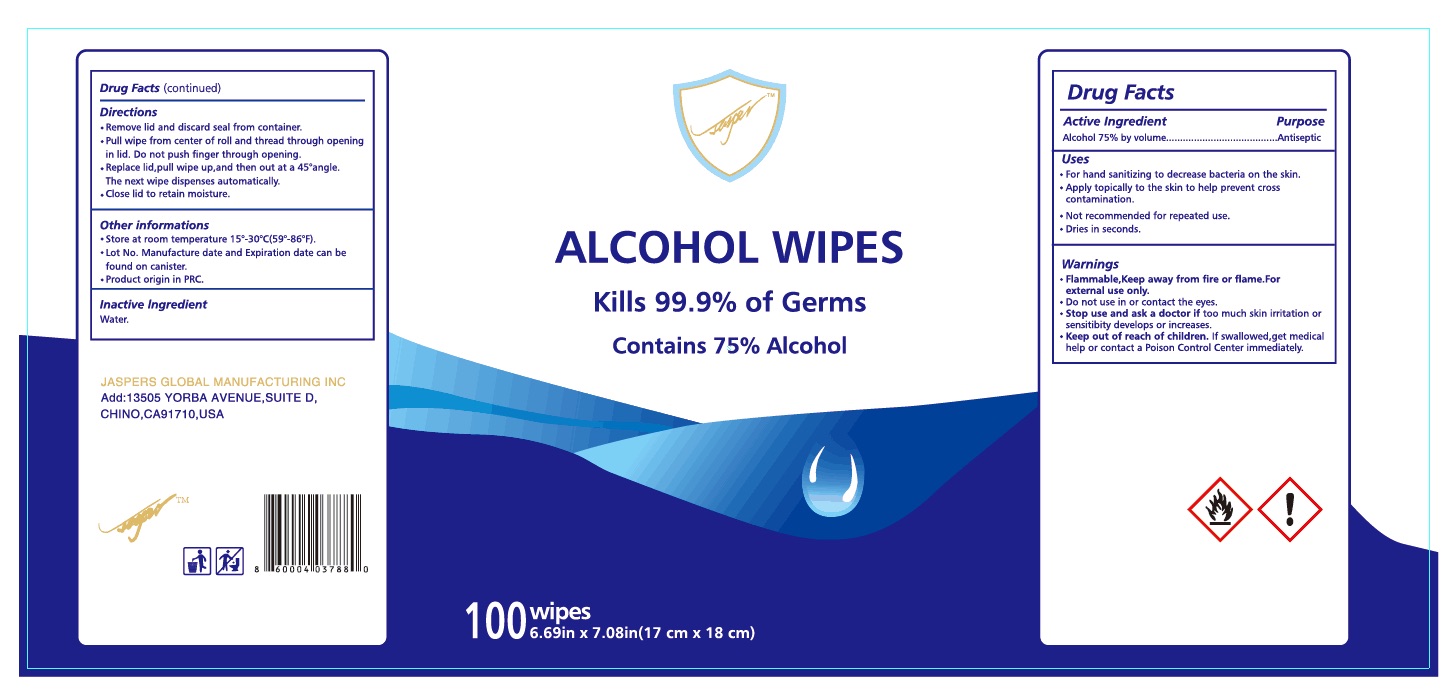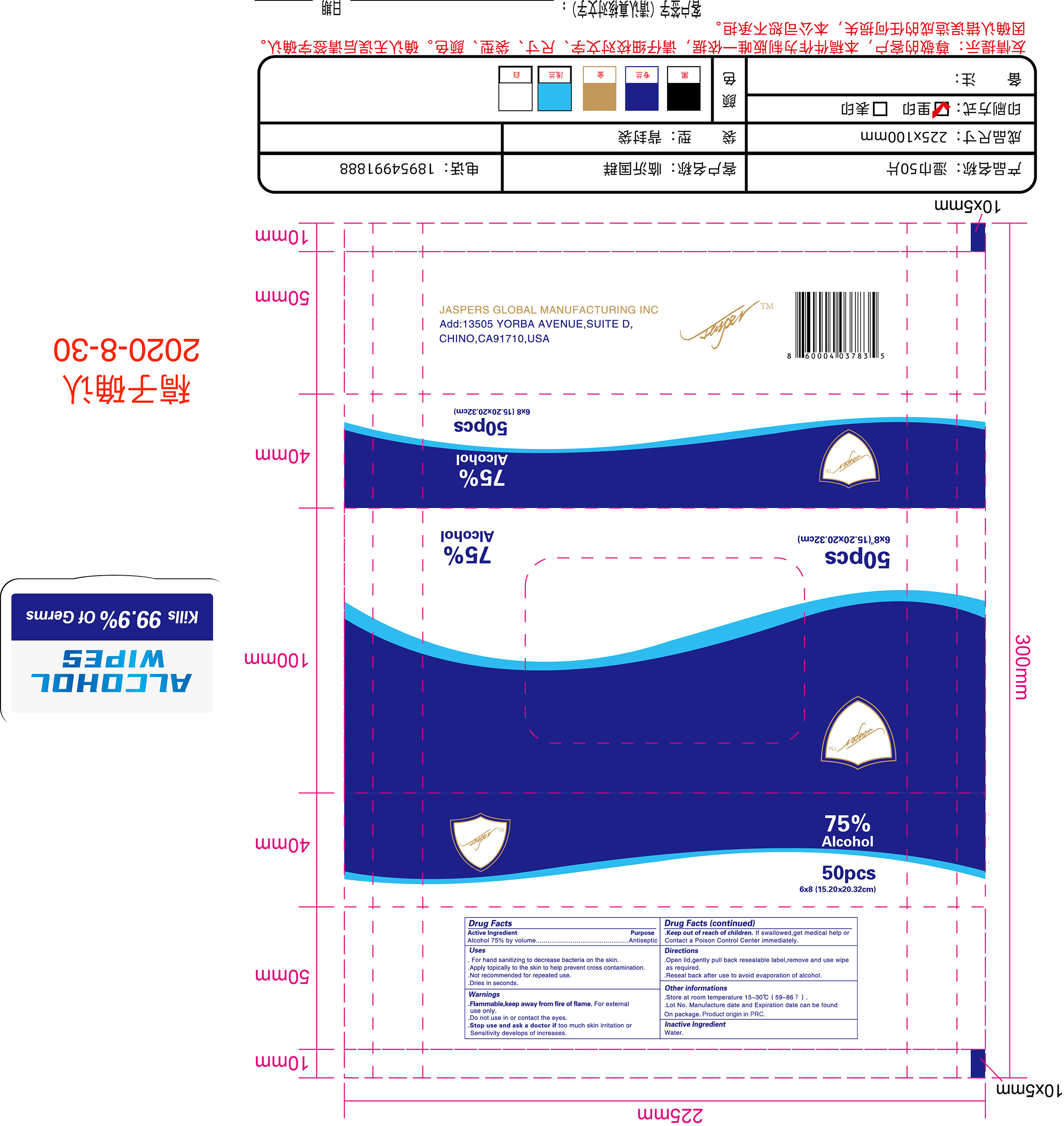 DRUG LABEL: Disinfection wipes
NDC: 79513-002 | Form: CLOTH
Manufacturer: LINYI WEIYESI DAILY CHEMICAL CO.,LTD
Category: otc | Type: HUMAN OTC DRUG LABEL
Date: 20200922

ACTIVE INGREDIENTS: ALCOHOL 0.75 1/1 1
INACTIVE INGREDIENTS: WATER

ACTIVE INGREDIENT(S)

Alcohol 70% v/v. Purpose: Antiseptic

PURPOSE

Antiseptic

USE

- For hand sanitizing to decrease bacteria on the skin.
- Apply topically to the skin to help prevent cross contamination.
- Not recommended for repeated use.
- Dries in seconds.

WARNINGS

- Flammable. Keep away from fire or flame. For external use only.
- Do not use in or contact the eyes.
- Stop use and ask a doctor if too much skin irritation or sensitivity develops of increases.

Keep out of reach of children. If swallowed, get medical help or contact a Poison Control Center immediately.

DIRECTIONS

- Open lid, gently pull back resealable label, remove and use wipe as required.
- Reseal back after use to avoid evaporation of alcohol.

OTHER INFORMATIONS

- Store at room temperature 15-30 ℃ (59-86℉)
- Lot No. manufacture date and expiration date can be found on package.

INACTIVE INGREDIENTS

Water

PACKAGE LABEL - PRINCIPAL DISPLAY PANEL

Disinfection wipes 50pcs 79513-002-50

Disinfection wipes 50pcs 79513-002-50

ALCOHOL WIPES 100 wipes 79513-003-00

ALCOHOL WIPES 50 wipes 79513-003-50